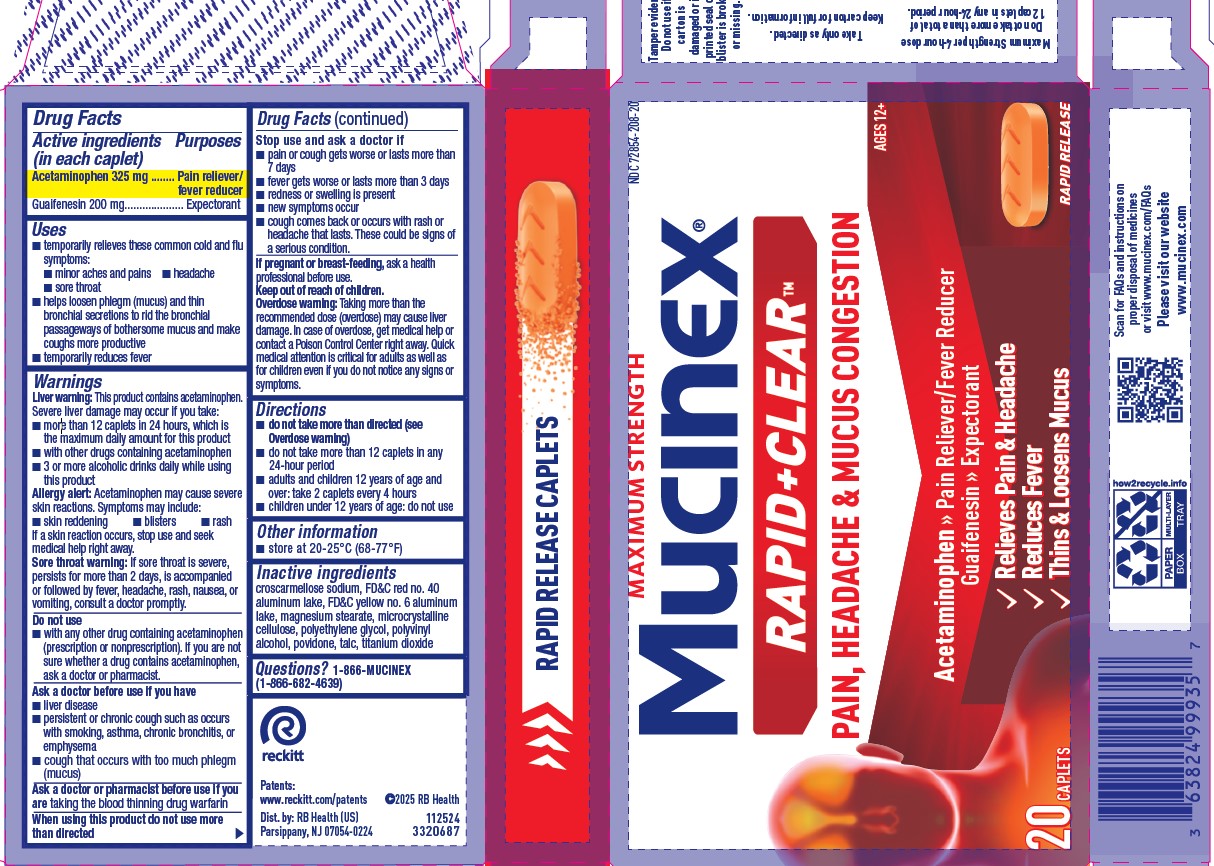 DRUG LABEL: Maximum Strength Mucinex Sinus-Max Pressure, Pain and Cough
NDC: 72854-208 | Form: TABLET, FILM COATED
Manufacturer: RB Health (US) LLC
Category: otc | Type: HUMAN OTC DRUG LABEL
Date: 20250513

ACTIVE INGREDIENTS: GUAIFENESIN 200 mg/1 1; ACETAMINOPHEN 325 mg/1 1
INACTIVE INGREDIENTS: TITANIUM DIOXIDE; MICROCRYSTALLINE CELLULOSE; POLYETHYLENE GLYCOL, UNSPECIFIED; POLYVINYL ALCOHOL; POVIDONE, UNSPECIFIED; CROSCARMELLOSE SODIUM; MAGNESIUM STEARATE; TALC; FD&C RED NO. 40 ALUMINUM LAKE; FD&C YELLOW NO. 6 ALUMINUM LAKE

Active ingredients
(in each caplet)

Acetaminophen 325 mg
Guaifenesin 200 mg

Uses
■ temporarily relieves these common cold and flu
symptoms:
■ minor aches and pains ■ headache
■ sore throat
■ helps loosen phlegm (mucus) and thin
bronchial secretions to rid the bronchial
passageways of bothersome mucus and make
coughs more productive
■ temporarily reduces fever

Warnings
Liver warning: This product contains acetaminophen.
Severe liver damage may occur if you take:
■ more than 12 caplets in 24 hours, which is
the maximum daily amount for this product
■ with other drugs containing acetaminophen
■ 3 or more alcoholic drinks daily while using
this product

Allergy alert: Acetaminophen may cause severe
skin reactions. Symptoms may include:
■ skin reddening ■ blisters ■ rash
If a skin reaction occurs, stop use and seek
medical help right away.

Sore throat warning: If sore throat is severe,
persists for more than 2 days, is accompanied
or followed by fever, headache, rash, nausea, or
vomiting, consult a doctor promptly.

Do not use
■ with any other drug containing acetaminophen
(prescription or nonprescription). If you are not
sure whether a drug contains acetaminophen,
ask a doctor or pharmacist.

Ask a doctor before use if you have
■ liver disease
■ persistent or chronic cough such as occurs
with smoking, asthma, chronic bronchitis, or
emphysema
■ cough that occurs with too much phlegm
(mucus)

Ask a doctor or pharmacist before use if you
are taking the blood thinning drug warfarin
When using this product do not use more
than directed

Stop use and ask a doctor if
■ pain or cough gets worse or lasts more than
7 days
■ fever gets worse or lasts more than 3 days
■ redness or swelling is present
■ new symptoms occur
■ cough comes back or occurs with rash or
headache that lasts. These could be signs of
a serious condition.

If pregnant or breast-feeding, ask a health
professional before use.
Overdose warning: Taking more than the
recommended dose (overdose) may cause liver
damage. In case of overdose, get medical help or
contact a Poison Control Center right away. Quick
medical attention is critical for adults as well as
for children even if you do not notice any signs or
symptoms.

Directions
■ do not take more than directed (see
Overdose warning)
■ do not take more than 12 caplets in any
24-hour period
■ adults and children 12 years of age and
over: take 2 caplets every 4 hours
■ children under 12 years of age: do not use

Other information
■ store at 20-25°C (68-77°F)

Inactive ingredients
croscarmellose sodium, FD&C red no. 40
aluminum lake, FD&C yellow no. 6 aluminum
lake, magnesium stearate, microcrystalline
cellulose, polyethylene glycol, polyvinyl
alcohol, povidone, talc, titanium dioxide

Questions? 1-866-MUCINEX
(1-866-682-4639)

PURPOSE

Acetaminophen 325 mg ........ Pain reliever/
fever reducer
Guaifenesin 200 mg.................... Expectorant

Keep out of reach of children.